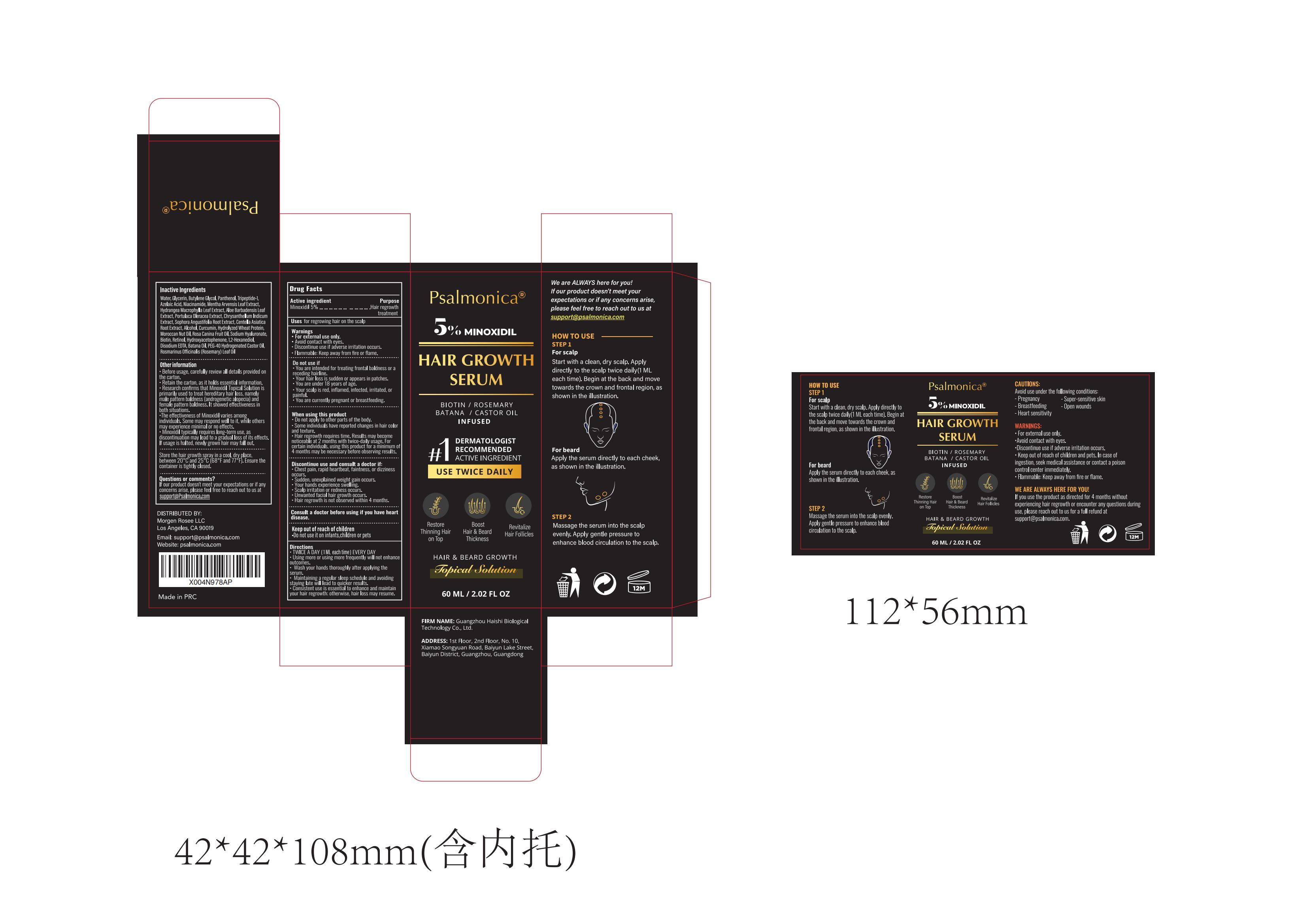 DRUG LABEL: Psalmonica Hair Growth Serum
NDC: 60771-0013 | Form: LIQUID
Manufacturer: Guangzhou Haishi Biological Technology Co., Ltd.
Category: otc | Type: HUMAN OTC DRUG LABEL
Date: 20250424

ACTIVE INGREDIENTS: MINOXIDIL 5 g/100 mL
INACTIVE INGREDIENTS: ROSA CANINA FRUIT OIL 1 g/100 mL; BUTYLENE GLYCOL 5 g/100 mL; PANTHENOL 1 g/100 mL; NIACINAMIDE 2 g/100 mL; CURCUMIN 0.5 g/100 mL; BIOTIN 1 g/100 mL; ALCOHOL 3 g/100 mL; AZELAIC ACID 2 g/100 mL; TRIPEPTIDE-1 2 g/100 mL; GLYCERIN 5 g/100 mL

Psalmonica Hair Growth Serum

Active ingredients

Minoxidil 5%

Purpose

Hair regrowth treatment

Uses

for regrowing hair on the scalp

Warnings

For external use only
Avoid contact with eyes.
Discontinue use if adverse irritation occurs.
Flammable: Keep away from fire or flame.

Stop use

Discontinue use if adverse irritation occurs.

Do not use

.You are intended for treating frontal baldness or areceding hairline.
.Your hair loss is sudden or appears in patchesYou are under 18 years of age.
.Your scalp is red, inflamed, infected, irritated, onpainful.
.You are currently pregnant or breastfeeding

When using this product

.Do not apply to other parts of the body.
.Some individuals have reported changes in hair colorand texture.
.Hair regrowth requires time. Results may becomenoticeable at 2 months with twice-daily usage. Forcertain individuals, using this product for a minimum of4 months may be necessary before observing results.

Keep out of reach of children.

Do not use it on infants,children or pets

Dosage

TWICE A DAY (1ML each time) EVERY DAY

Inactive ingredients

WATER 58.425%
GLYCERIN 5%
BUTYLENE GLYCOL 5%
PANTHENOL 1%
TRIPEPTIDE-1 2%
AZELAIC ACID 2%
NIACINAMIDE 2%
MENTHA ARVENSIS LEAF EXTRACT 0.83%
HYDRANGEA MACROPHYLLA LEAF EXTRACT 0.83%
ALOE BARBADENSIS LEAF EXTRACT 0.83%
PORTULACA OLERACEA EXTRACT 0.83%
CHRYSANTHELLUM INDICUM EXTRACT 0.84%
SOPHORA ANGUSTIFOLIA ROOT EXTRACT 0.84%
CENTELLA ASIATICA ROOT EXTRACT 2%
ALCOHOL 3%
CURCUMIN 0.5%
HYDROLYZED WHEAT PROTEIN 2%
MOROCCAN NUT OIL 2%
ROSA CANINA FRUIT OIL 1%
SODIUM HYALURONATE 1%
BIOTIN 1%
RETINOL 0.025%
HYDROXYACETOPHENONE 0.5%
1,2-HEXANEDIOL 0.5%
DISODIUM EDTA 0.05%
BATANA OIL 0.5
PEG-40 HYDROGENATED CASTOR OIL 0.4%
ROSMARINUS OFFICINALIS (ROSEMARY) LEAF OIL 0.1%